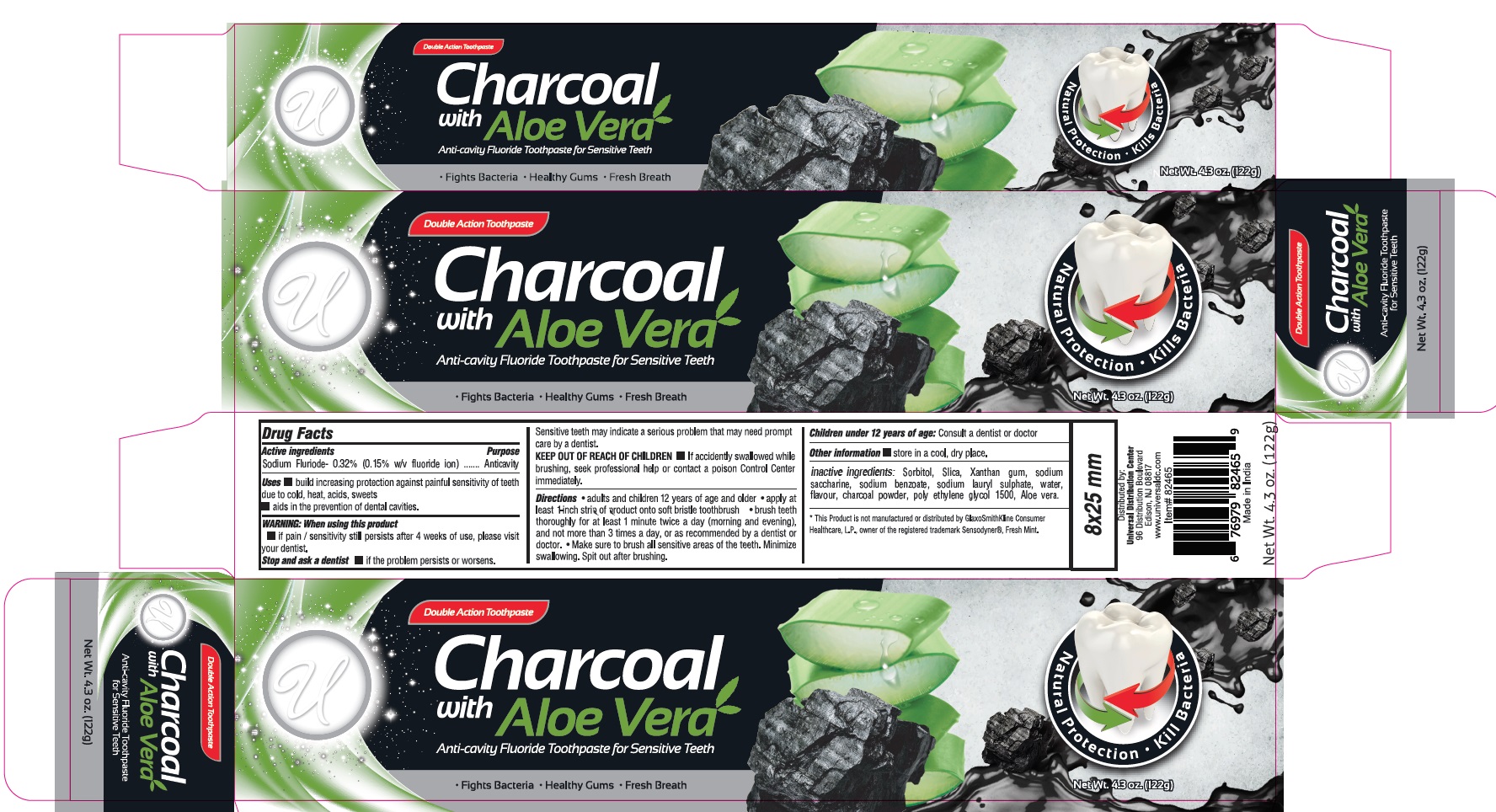 DRUG LABEL: UNIVERSAL CHARCOAL WITH ALOE VERA ANTI-CAVITY FLUORIDE
NDC: 52000-110 | Form: PASTE
Manufacturer: Universal Distribution Center LLC
Category: otc | Type: HUMAN OTC DRUG LABEL
Date: 20231116

ACTIVE INGREDIENTS: SODIUM FLUORIDE 0.15 g/100 g
INACTIVE INGREDIENTS: SORBITOL; SILICON DIOXIDE; XANTHAN GUM; SACCHARIN SODIUM; SODIUM BENZOATE; SODIUM LAURYL SULFATE; WATER; ACTIVATED CHARCOAL; POLYETHYLENE GLYCOL 1600; ALOE VERA LEAF

UNIVERSAL CHARCOAL WITH ALOE VERA ANTI-CAVITY FLUORIDE TOOTHPASTE

Active Ingredient

Sodium Fluoride-0.32% (0.15% w/v fluride ion)

Purpose

Anticavity

Uses

- builds increasing protection against painful sensitivity of teeth due to cold, heat, acids, sweets
- aids in the prevention of dental cavities.

Warning

When using this product

- if pain\ sensitivity still persists after 4 weeks of use, please visit your dentist.

Stop and ask a dentist

- if the problem persists or worsens.

Sensitivity teeth may indicate a serious problem that may need prompt care by a dentist.

Keep out of reach of children

- If accidentally swallowed while brushing, seek professional help or contact a Poison Control Center immediately.

Directions

- adults and children 12 years of age and older
- apply atleast 1-inch strip of product onto soft bristle toothbrush
- brush teeth thoroughly for atleast 1 minute twice a day (morning and evening), and not more then 3 times a day, or as recommended by a dentist or doctor.
- Make sure to brush all sensitive areas of the teeth. Minimize swallowing. Spit out after brushing.

Children under 12 years of age: Consult a dentist or doctor

Other information

- store in a cool, dry place.

Inactive Ingredients

Sorbitol, Silica, Xanthan gum, Sodium saccharine, Sodium benzoate, Sodium Lauryl sulphate, Water, Flavor, Charcoal powder, poly ethylene glycol 1500, Aloe vera.

PACKAGE LABEL

PRINCIPAL DISPLAY PANEL

UNIVERSAL CHARCOAL WITH ALOE VERA ANTI-CAVITY FLUORIDE TOOTHPASTE